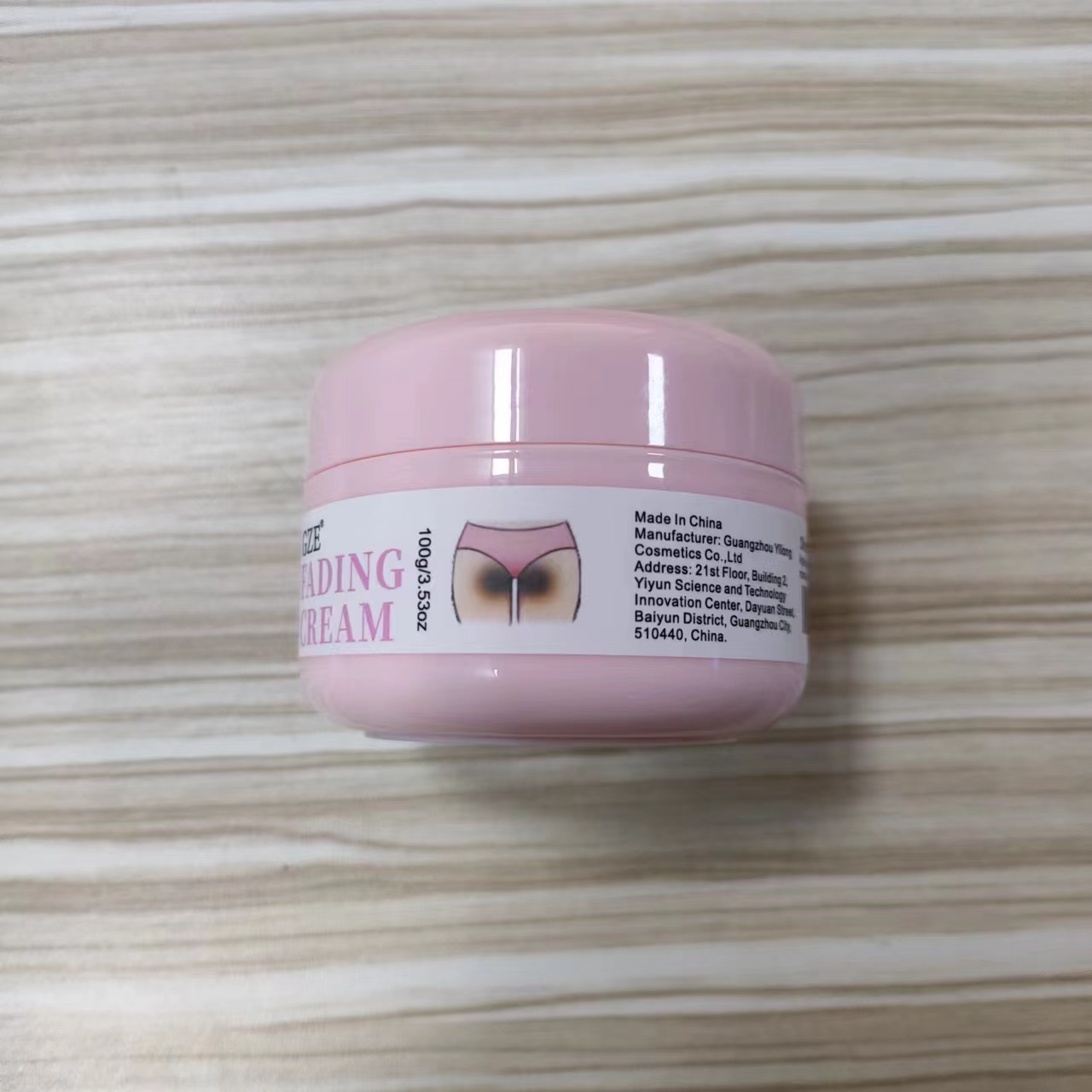 DRUG LABEL: GZE Fading Cream
NDC: 74458-234 | Form: CREAM
Manufacturer: Guangzhou Yilong Cosmetics Co., Ltd
Category: otc | Type: HUMAN OTC DRUG LABEL
Date: 20241031

ACTIVE INGREDIENTS: NIACINAMIDE 4.05 g/100 g; RETINOL 0.15 g/100 g
INACTIVE INGREDIENTS: THEOBROMA CACAO (COCOA) SEED BUTTER; AQUA; ASCORBIC ACID; TOCOPHEROL

GZE FADING CREAM

ACTIVE INGREDIENT

Niacinamide

Retinol

INACTIVE INGREDIENT

Aqua

Theobroma Cacao (Cocoa) Seed Butter

Ascorbic Acid

Tocopherol

PURPOSE

Body whitening.

INDICATIONS AND USAGE

Apply generously all over body morning and night.

WARNINGS

For external use only.

Stop use and ask a doctor if rash occurs.

Do not use on damaged or broken skin.

When using this product keep out of eyes. Rinse with water to remove.

Keep out of reach of children. If swallowed, get medical help or contact a Poison Control Center right away.

DOSAGE AND ADMINISTRATION

Apply generously all over body morning and night.